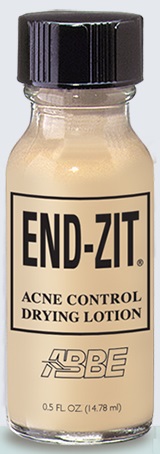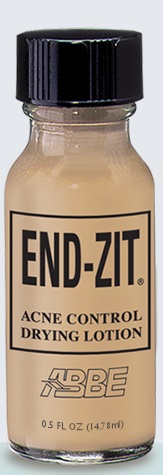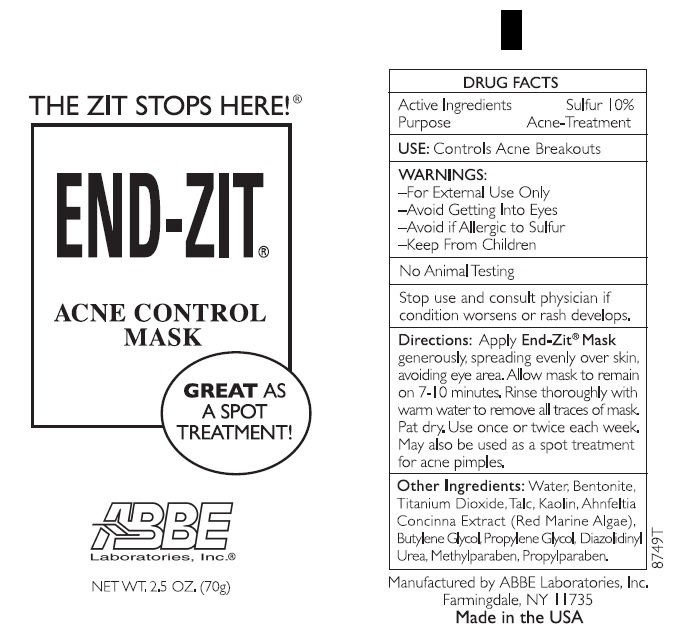 DRUG LABEL: END-ZIT
NDC: 68605-2001 | Form: LOTION, AUGMENTED
Manufacturer: ABBE Laboratories, Inc.
Category: otc | Type: HUMAN OTC DRUG LABEL
Date: 20260113

ACTIVE INGREDIENTS: SULFUR .05 g/1 mL
INACTIVE INGREDIENTS: ISOPROPYL ALCOHOL; WATER; ZINC OXIDE; PROPYLENE GLYCOL; CAMPHOR (SYNTHETIC); TALC; SODIUM LAURETH SULFATE; TITANIUM DIOXIDE; DIAZOLIDINYL UREA; METHYLPARABEN; PROPYLPARABEN

END-ZIT® ACNE CONTROL DRYING LOTION

INDICATIONS AND USAGE

Intended for use on blemishes only. This advanced formulation is designed to dry and aid in elimination of pimples. It is make-up quality for excellent coverage of the blemish. It is unbelievably effective, clinically tested, dermatologist approved and recommended.

DOSAGE AND ADMINISTRATION

DIRECTIONS: Shake bottle well before each use. Apply directly to blemish only, using applicator. Wait a few moments until slightly dry. Pat with fingertip or clean cotton swab to blend color to skin. Make-up may be applied if desired. Should remain on skin all day. Re-apply at night to clean skin to remain on skin overnight.

DO NOT USE

NOTE: PERSONS WITH KNOWN SENSITIVITY TO SULFUR SHOULD AVOID USE OF THIS PRODUCT.
KEEP FROM EYES.

DRUG FACTS
ACTIVE INGREDIENT ............ SULFUR 5%

PURPOSE ............. ACNE TREATMENT

WARNINGS:
• For external use only.
• Using other topical acne medications at the same time or immediately following use of this product may increase dryness or irritation of the skin. If this occurs, only one medication should be used unless directed by a doctor.
• Do not get into eyes. If excessive skin irritation deve lops or increases, discontinue use and consult a doctor.

• Keep out of reach of children.

INACTIVE INGREDIENT

OTHER INGREDIENTS: Isopropyl Alcohol, Water, Zinc Oxide, Propylene Glycol, Camphor, Talc, Sodium Laureth Sulfate, Titanium Dioxide, Diazolidinyl Urea, Methylparaben, Propylparaben. May contain Iron Oxides.

NDC #'s
Light/Medium 68605-2001-2 Medium/Dark 68605-2002-2 Acne Control Mask 68605-2010-2

———PACKAGE LABEL.PRINCIPAL DISPLY PANEL———

DIRECTIONS: SHAKE BOTTLE WELL.
APPLY TWICE DAILY DIRECTLY TO
ACNE BREAKOUT. ALLOW TO DRY
FOR 10 SECONDS. PAT TO BLEND.
APPLY MAKE-UP IF DESIRED.
ACTIVE INGREDIENT: SULFUR 5%.

WARNINGS:
AVOID IF ALLERGIC TO SULFUR
AVOID CONTACT WITH EYES
FOR EXTERNAL USE ONLY
KEEP FROM CHILDREN
Manufactured by ABBE Laboratories, Inc.
Farmingdale, NY 11735
Made in the U.S.A.
END-ZIT®
ACNE CONTROL
DRYING LOTION
ABBE
0.5 OZ. (14.78 g)

———PACKAGE LABEL.PRINCIPAL DISPLY PANEL———

DIRECTIONS: SHAKE BOTTLE WELL.
APPLY TWICE DAILY DIRECTLY TO
ACNE BREAKOUT. ALLOW TO DRY
FOR 10 SECONDS. PAT TO BLEND.
APPLY MAKE-UP IF DESIRED.
ACTIVE INGREDIENT: SULFUR 5%.

WARNINGS:
AVOID IF ALLERGIC TO SULFUR
AVOID CONTACT WITH EYES
FOR EXTERNAL USE ONLY
KEEP FROM CHILDREN
Manufactured by ABBE Laboratories, Inc.
Farmingdale, NY 11735
Made in the U.S.A.
END-ZIT®
ACNE CONTROL
DRYING LOTION
ABBE
2.5 OZ. (70 g)